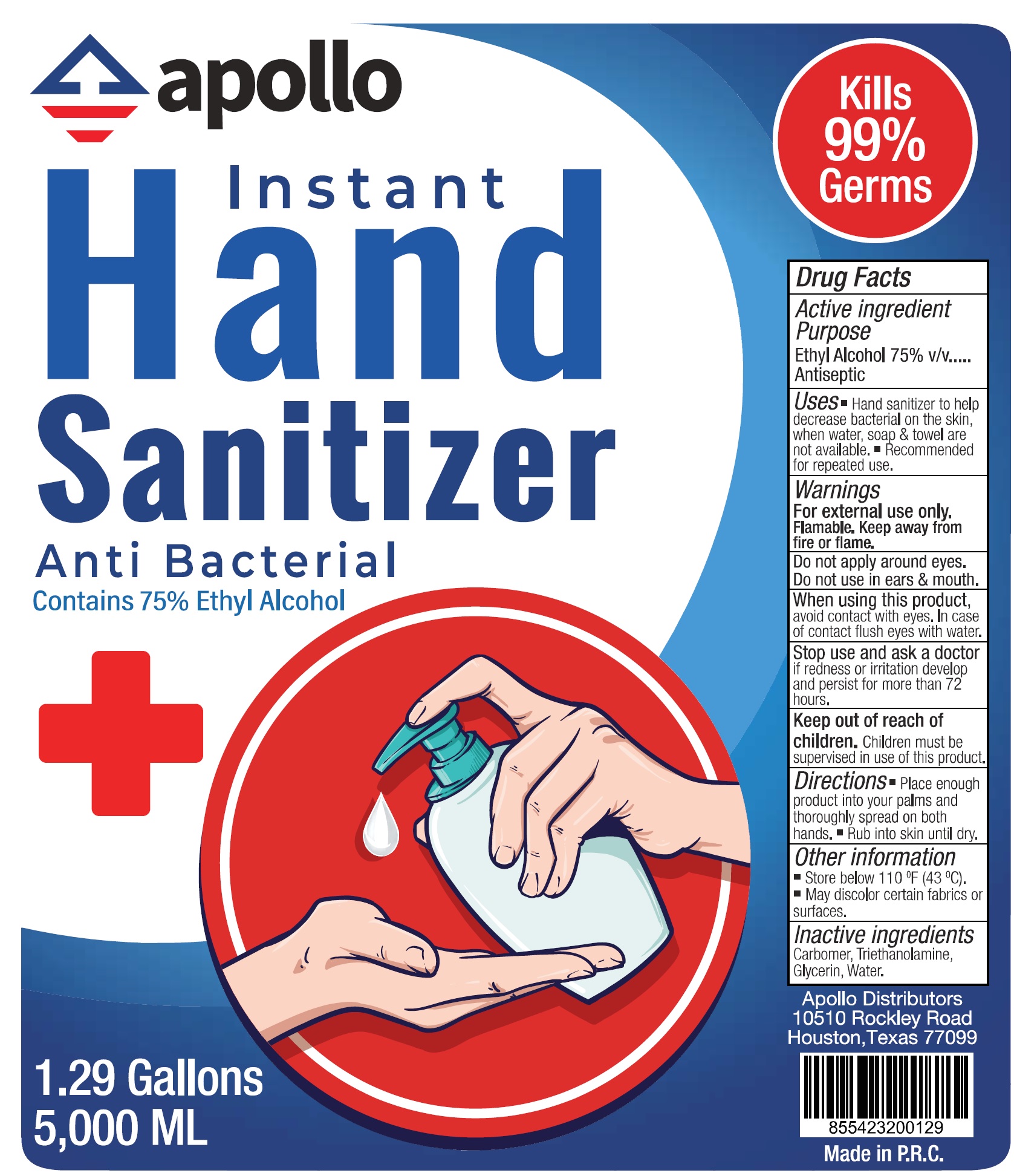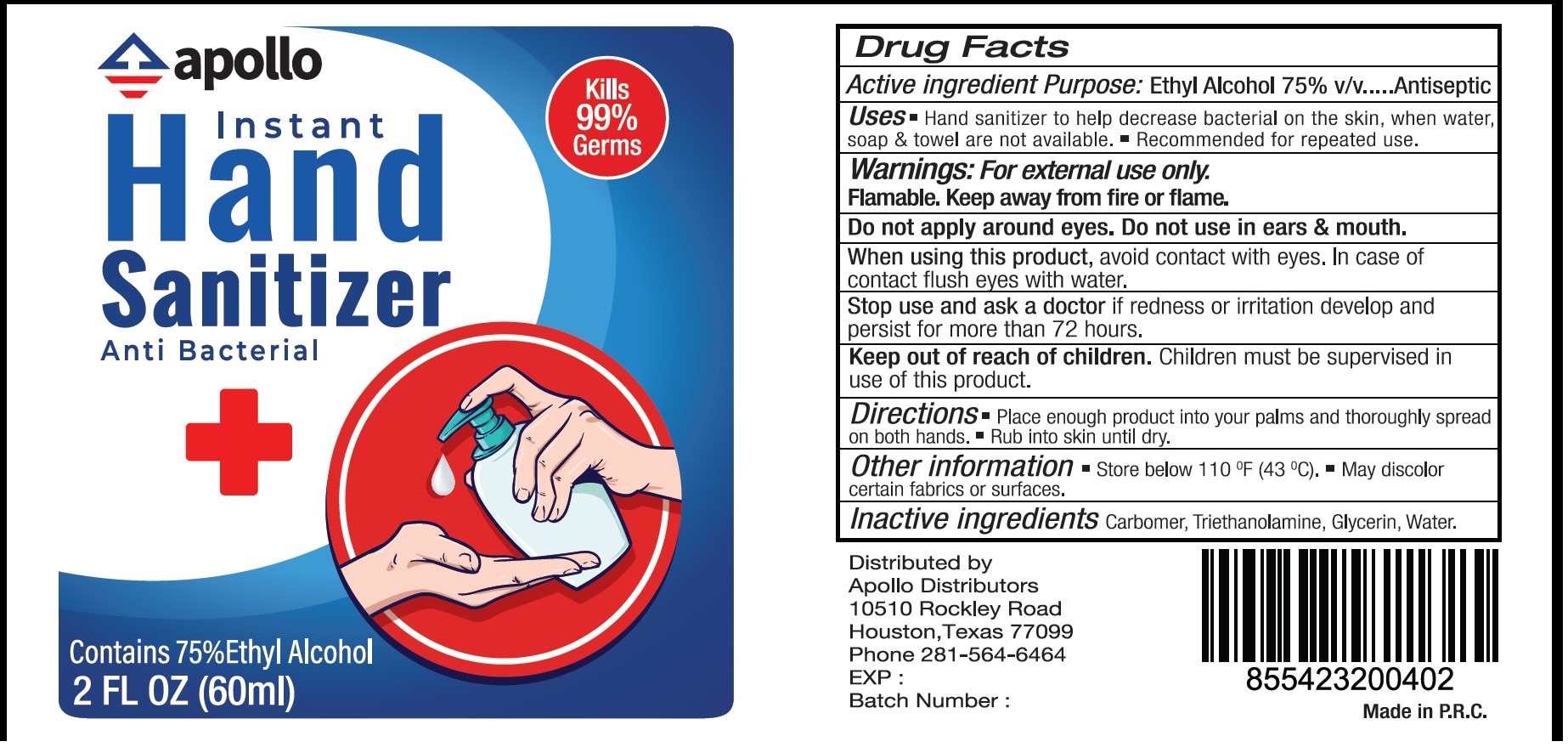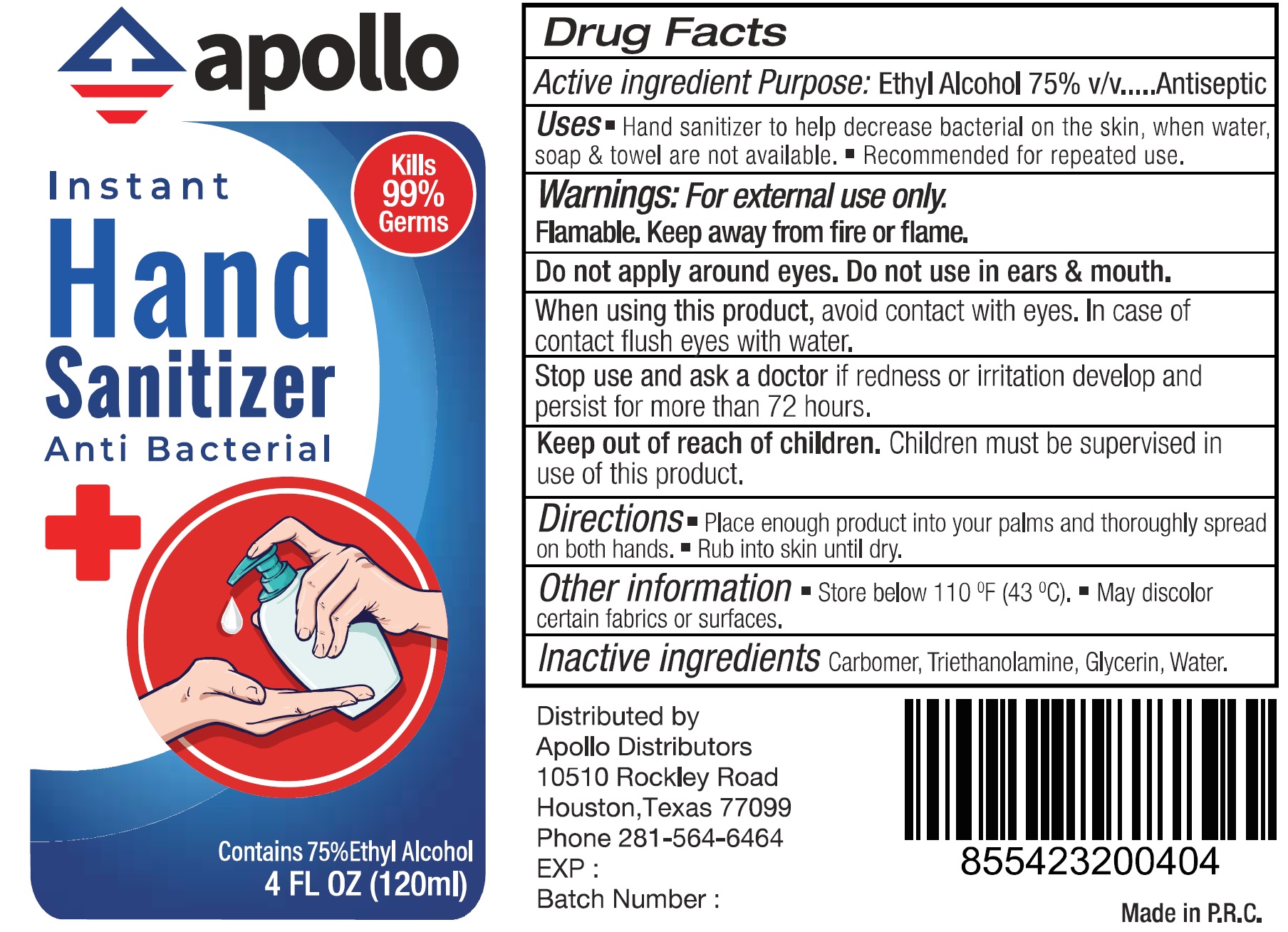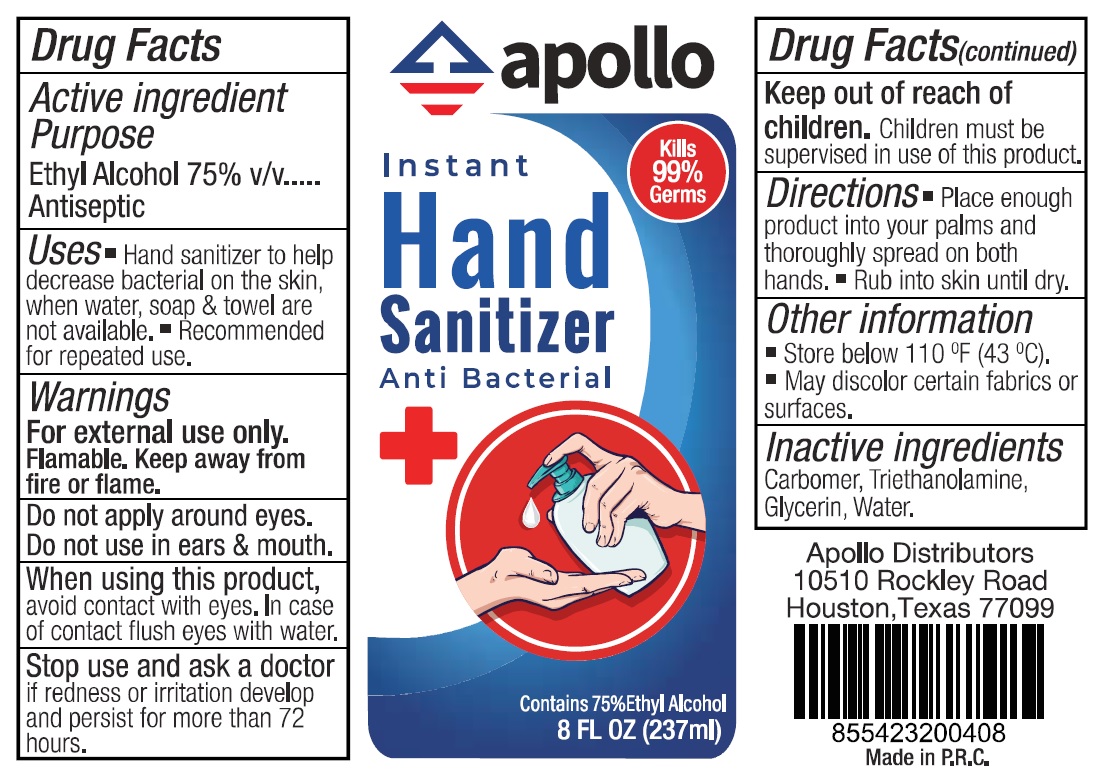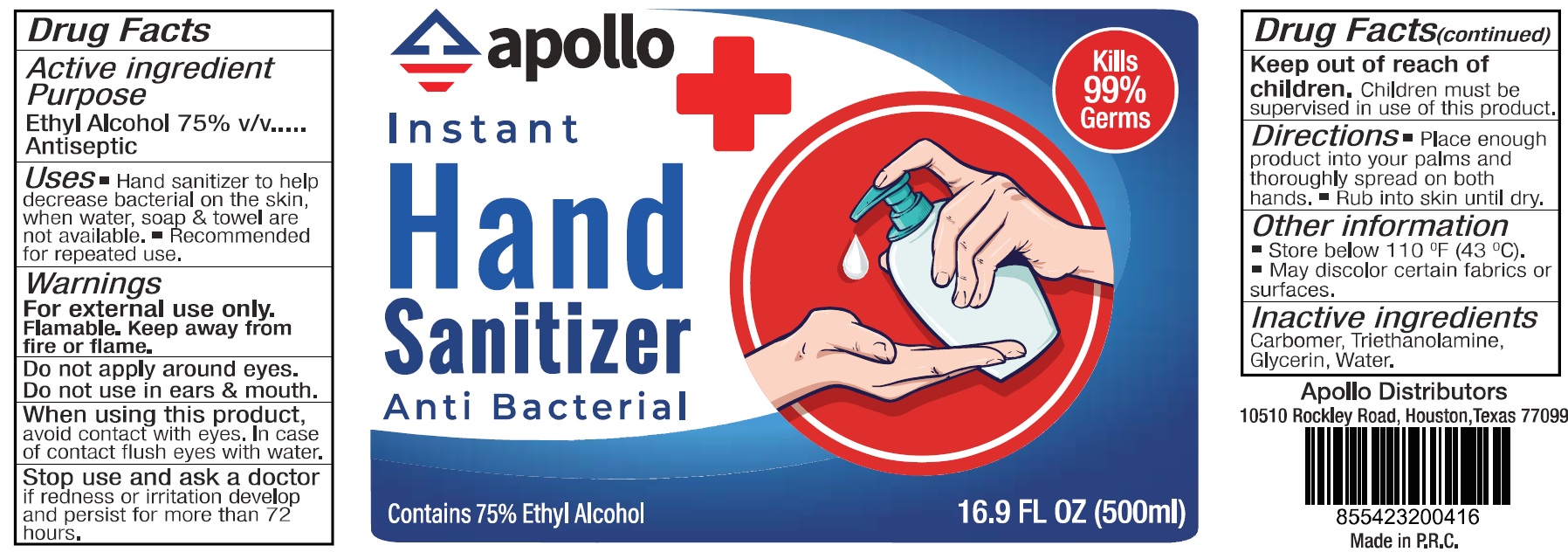 DRUG LABEL: Apollo Instant Hand Sanitizer
NDC: 78303-000 | Form: GEL
Manufacturer: Sbu Group L.P. DBA Apollo Distributors
Category: otc | Type: HUMAN OTC DRUG LABEL
Date: 20200714

ACTIVE INGREDIENTS: ALCOHOL 0.75 1/1 mL
INACTIVE INGREDIENTS: CARBOMER HOMOPOLYMER, UNSPECIFIED TYPE; TROLAMINE; GLYCERIN; WATER

Apollo Instant Hand Sanitizer

Active ingredient

Ethyl Alcohol 75% v/v

Purpose

Antiseptic

Uses

- Hand sanitizer to help decrease bactrerial on the skin, when water, soap & towel are not available.
- Recommended for repeated use.

Warnings

For external use only. Flammable. Keep away from fire or flame.

Do not apply around eyes. Do not use in ears & mouth.

When using this product,

avoid contact with eyes. In case of contact flush eyes with water.

Stop use and ask a doctor

if redness or irritation develop and persists for more than 72 hours.

Keep out of reach of children.

Children must be supervised in use of this product.

Directions

- Place enough product into your palms and thoroughly spread on both hands.
- Rub into skin until dry.

Other information

- Store below 110 °F (43 °C).
- May discolor certain fabrics or surfaces.

Inactive ingredients

Carbomer, Triethanolamine, Glycerin, Water.